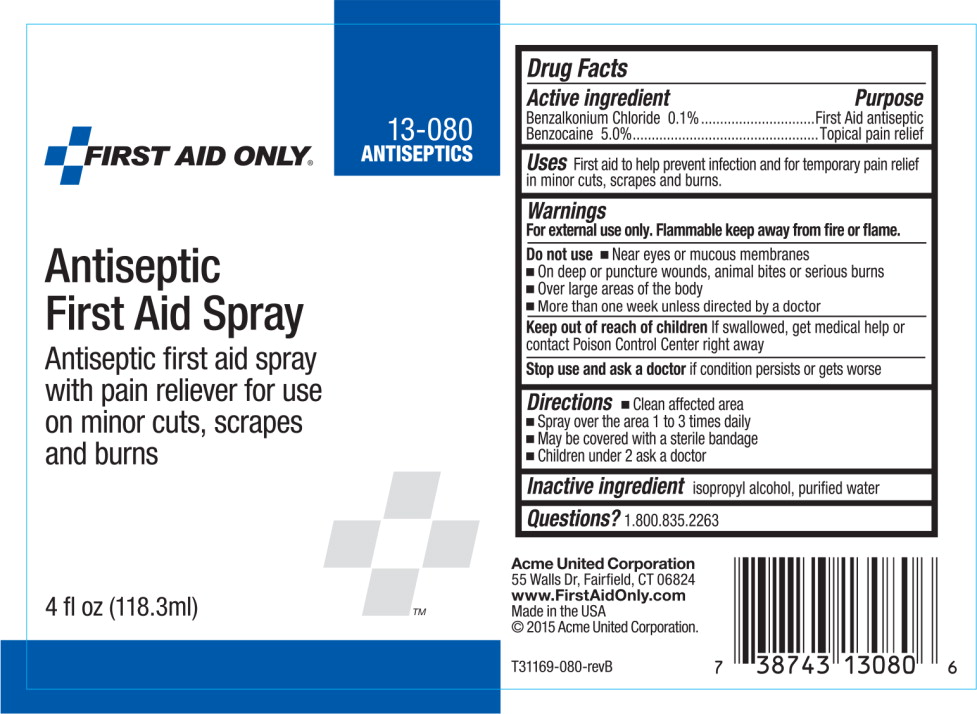 DRUG LABEL: Antiseptic First Aid
NDC: 0924-0931 | Form: SPRAY
Manufacturer: Acme United Corp
Category: otc | Type: HUMAN OTC DRUG LABEL
Date: 20141006

ACTIVE INGREDIENTS: benzalkonium chloride 1 mg/1 g; benzocaine 50 mg/1 g
INACTIVE INGREDIENTS: isopropyl alcohol; water

Drug Facts

Active ingredients

Benzalkonium Chloride 0.1 %

Benzocaine 5.0%

Purpose

First aid antiseptic

Topical pain relief

Uses

First aid to help prevent infection and for temporary pain relief in minor cuts, scrapes and burns

Warnings

For external use only. Flammable keep away from fire or flame

Do not use

- near eyes or mucous membranes
- on deep or puncture wounds, animal bites, or serious burns
- over large areas of the body
- more than one week unless directed by a doctor

Keep out of reach of children. If swallowed, get medical help or contact a Poison Control Center right away.

Stop use and ask a doctor if condition persists or gets worse

Directions

- clean affected area
- spray over the area 1 to 3 times daily
- may be covered with a sterile bandage
- children under 2 ask a doctor

Inactive ingredients

isopropyl alcohol, purified water

Questions?

call 203-857-5361

Principal Display Panel - Bottle Label

13-080

ANTISEPTICS

FIRST AID ONLY®

Antiseptic
First Aid Spray

Antiseptic first aid spray
with pain reliever for use
on minor cuts, scrapes
and burns

4 fl oz (118.3ml)